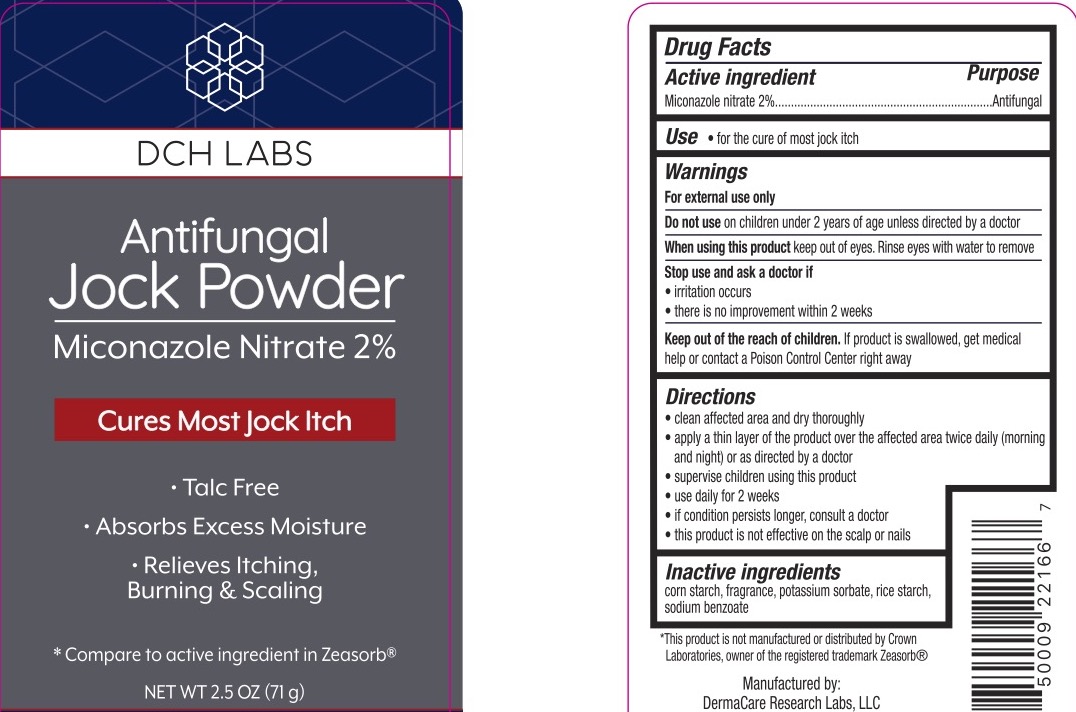 DRUG LABEL: DCH Labs  Antifungal Jock
NDC: 72839-096 | Form: POWDER
Manufacturer: Derma Care Research Labs, LLC
Category: otc | Type: HUMAN OTC DRUG LABEL
Date: 20250127

ACTIVE INGREDIENTS: MICONAZOLE NITRATE 2 g/100 g
INACTIVE INGREDIENTS: SODIUM BENZOATE; STARCH, CORN; POTASSIUM SORBATE; STARCH, RICE

DCH Labs Antifungal Jock Powder

ACTIVE INGREDIENT

Miconazole Nitrate 2%

PURPOSE

Antifungal

INDICATIONS AND USAGE

For the cure of athlete's foot and jock itch. Relieves itching and chafing associated with jock itch.

WARNINGS

For external use only. Do not use on children under 2 years of age unless directed by a doctor or for diaper rash. When using thisproduct avoid contact with the eyes. Stop use and ask a doctor if irritation occurs or if there is no improvement within 2 weeks.

KEEP OUT OF REACH OF CHILDREN

If swallowed, get medical help or contact a Poison Control Center right away.

DOSAGE AND ADMINISTRATION

Cleanse the affected area and dry thoroughly. Apply a thin layer of the product over the affected area twice daily or as directed by a doctor or healthcare professional. Supervise children in the use of this product.

Use daily for 2 weeks.

If the condition persists, consult a doctor.

This product is not effective on the scalp or nails.

INACTIVE INGREDIENT

Corn Starch, Fragrance, Potassium Sorbate, Rice Starch, Sodium Benzoate.